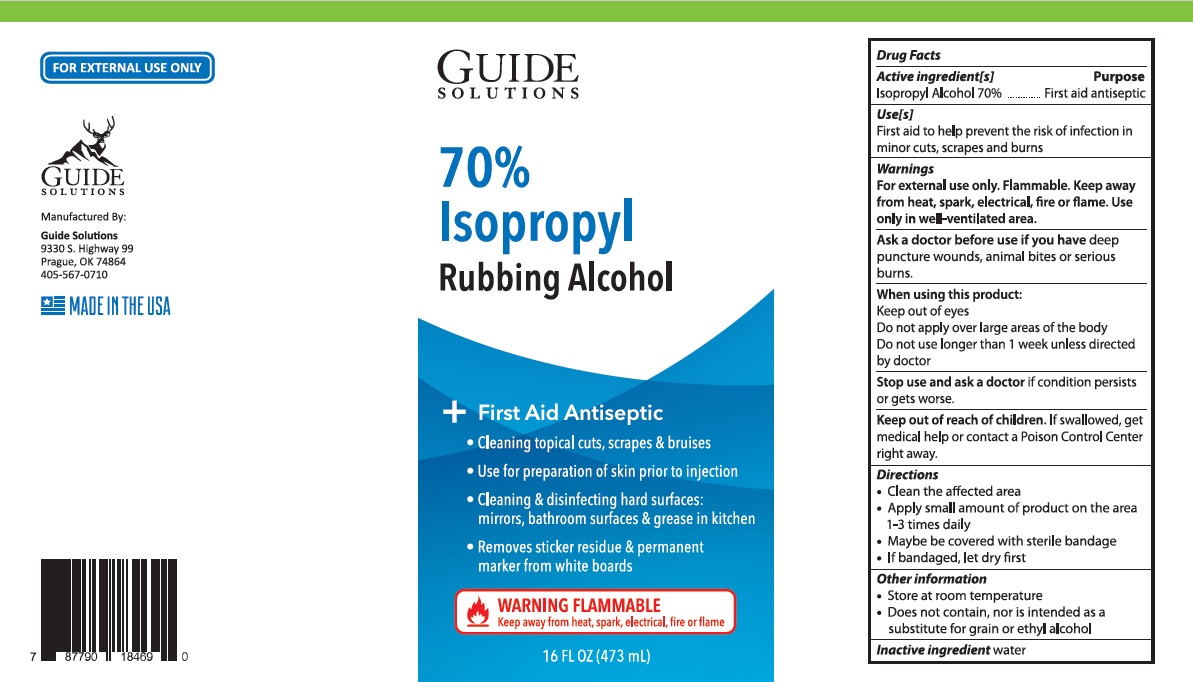 DRUG LABEL: 70% Isopropyl Rubbing Alcohol
NDC: 77042-101 | Form: LIQUID
Manufacturer: Guide Energy Solutions LLC
Category: otc | Type: HUMAN OTC DRUG LABEL
Date: 20201026

ACTIVE INGREDIENTS: ISOPROPYL ALCOHOL 70 mL/100 mL
INACTIVE INGREDIENTS: WATER

70% Isopropyl Rubbing Alcohol

Active ingredient[s]

Isopropyl Alcohol 70%

Purpose

First aid antiseptic

Use[s]

First aid to help prevent the risk of infection in minor cuts, scraps and burns

Warnings

For external use only. Flammable. Keep away from heat, spark, electrical, fire or flame. Use only in well-ventilated area.

Ask a doctor before use if you have deep puncture wounds, animal bites or serious burns.

When using this product:

keep out of eyes

Do not apply over large areas of the body

Do not use longer than 1 week unless directed by doctor

Stop use and ask a doctor if condition persists or gets worse.

Keep out of reach of children. If swallowed, get medical help or contact a Poison Control Center right away.

Directions

- Clean the affected area
- Apply small amount of product on the area 1-3 times daily
- May be covered with sterile bandage
- If bandaged, let dry first

Other information

- Store at room temperature
- Does not contain, nor is intended as a substitute for grain or ethyl alcohol

Inactive ingredient

water

+ First aid Antiseptic

• Cleaning topical cuts, scrapes & bruises

• Use for preparation of skin prior to injection

• Cleaning & disinfecting hard surfaces: mirrors, bathroom surfaces & grease in kitchen

• Removes sticker residue & permanent marker from white boards

WARNING FLAMMABLE

Keep away from heat, spark, electrical, fire or flame

FOR EXTERNAL USE ONLY

Manufactured By:

Guide Solutions

9330 S. Highway 99

Prague, OK 74864

405-567-0710

MADE IN THE USA